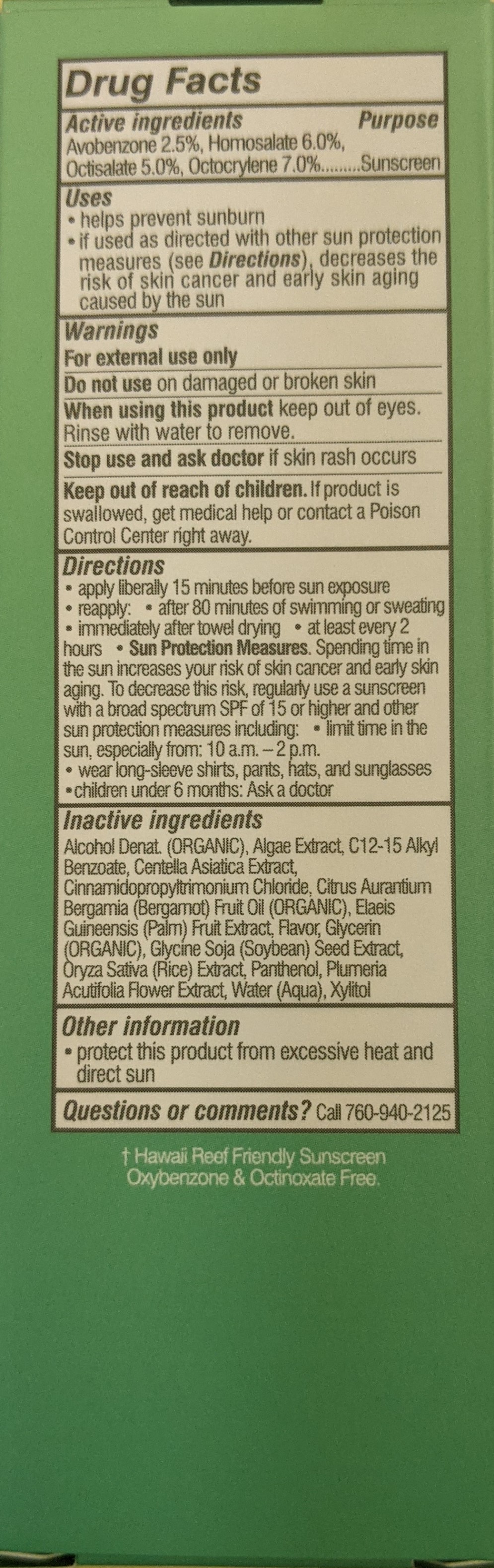 DRUG LABEL: ScalpHair MistSunscreen SPF30
NDC: 79753-039 | Form: SPRAY
Manufacturer: COOLA LLC
Category: otc | Type: HUMAN OTC DRUG LABEL
Date: 20251008

ACTIVE INGREDIENTS: HOMOSALATE 3.6 g/60 mL; OCTISALATE 3 g/60 mL; AVOBENZONE 1.5 g/60 mL; OCTOCRYLENE 4.2 g/60 mL
INACTIVE INGREDIENTS: ALCOHOL 44.9 g/60 mL

COOLA & Hair Mist Organic Sunscreen SPF 30

Active Ingredients

Avobenzone 2.50%

Homosalate 6.00%

Octisalate 5.00%

Octocrylene 7.00%

Purpose

Sunscreen

Uses

■ helps prevent sunburn

■ if used as directed with other sun protection measures

■ decreases the risk of skin cancer and early skin aging caused by the sun

Warnings

■ For external use only

■ Do not use on damaged or broken skin

■ When using this product keep out of eyes. Rinse with water to remove.

■ Stop use and contact a doctor if rash occurs

■ Keep out of reach of children. If swallowed, get medical help or contact a Poison Control Center immediately.

Directions

■ apply liberally and evenly 15 minutes before sun exposure ■ reapply:

■ after 80 minutes of swimming or sweating

■ immediately after towel drying

■ at least every 2 hours

■ Sun Protection Measures. Spending time in the sun increases your risk of skin cancer and early skin aging. To decrease this risk, regularly use a sunscreen with a Broad-Spectrum SPF value of 15 or higher and other sun protection measures including:

■ limit time in the sun, especially from 10 a.m. – 2 p.m.

■ wear long-sleeved shirts, pants, hats, and sunglasses

■ children under 6 months of age: ask a doctor

Storage and Handling

Protect the product in this container from excessive heat and direct sun.

Inactive Ingredients

Alcohol Denat (Organic)., Algae Extract, C12-15 Alkyl Benzoate, Centella Asiatica Extract, Cinnamidopropyltrimonium Chloride, Citrus Aurantium Bergamia (Bergamot) Fruit Oil (Organic), Elaeis Guineensis (Palm) Fruit Extract, Flavor, Glycerin (Organic), Glycine Soja (Soybean) Seed Extract, Oryza Sativa (Rice) Extract, Panthenol, Plumeria Acutifolia Flower Extract, Water (Aqua), Xylitol

Questions or Comments

Call 760-940-2125

Dosage & Administration

Apply liberally to areas exposed to sun.